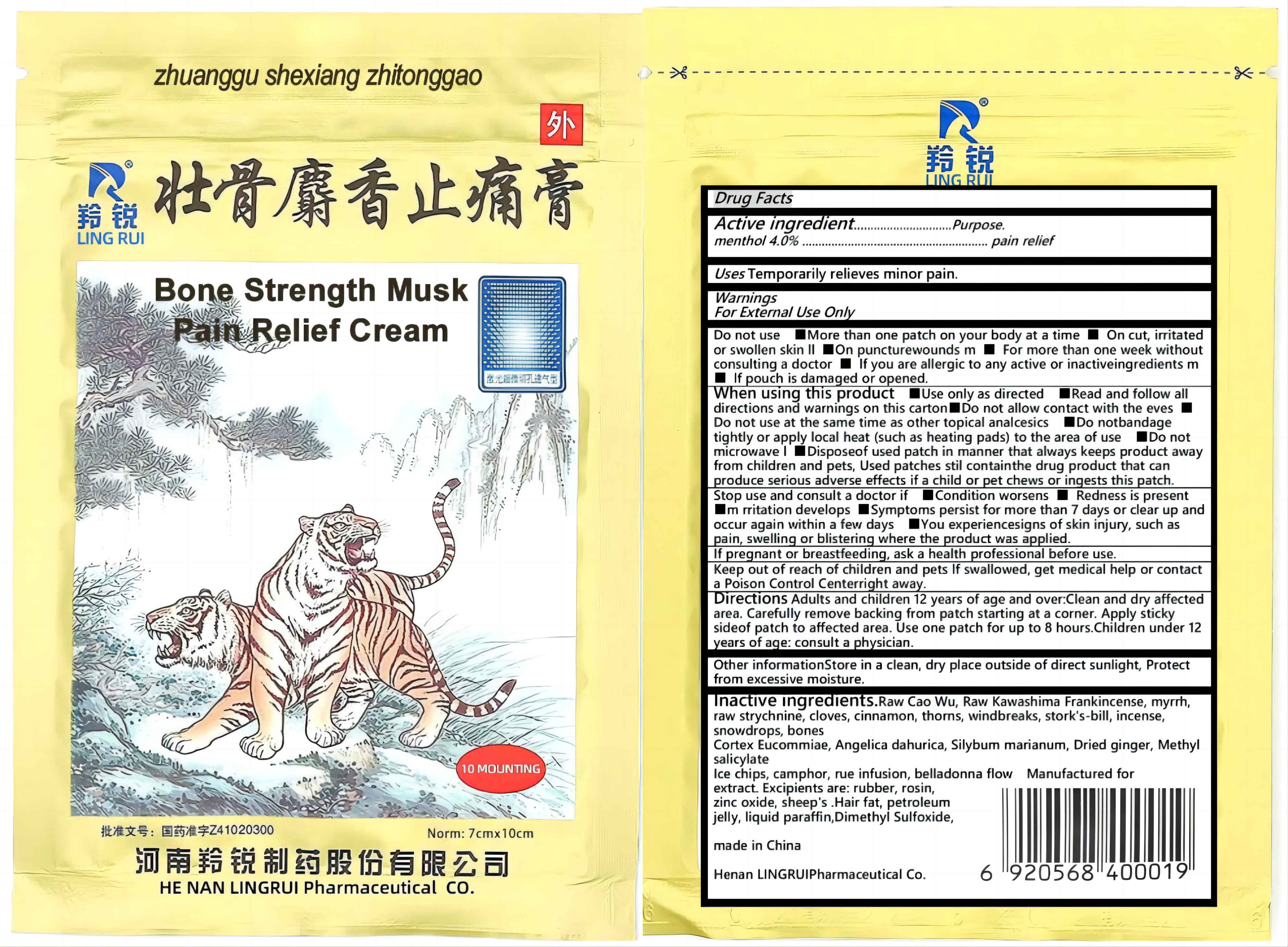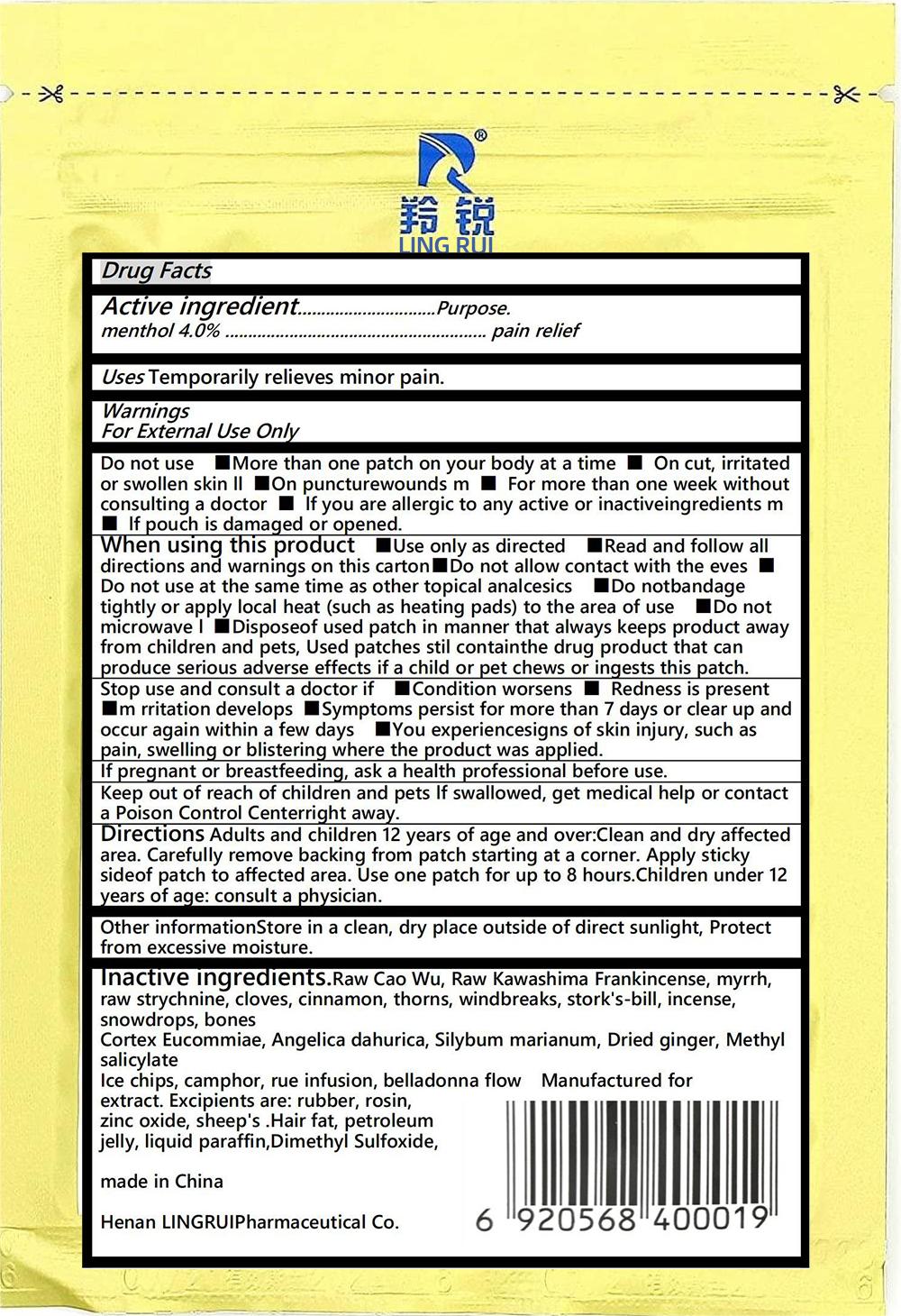 DRUG LABEL: LINGRUI Bone Strength Musk Pain Relief Cream
NDC: 83806-001 | Form: PATCH
Manufacturer: Dengfeng City Jucai Trading Co., LTD
Category: otc | Type: HUMAN OTC DRUG LABEL
Date: 20231119

ACTIVE INGREDIENTS: MENTHOL 4 g/100 1
INACTIVE INGREDIENTS: STRYCHNINE; CALOCEDRUS DECURRENS POLLEN; ANGELICA DAHURICA ROOT; GINGER; METHYL SALICYLATE; BORNEOL; CAMPHOROSMA MONSPELIACA WHOLE; VANILLA; WATER; ZINC OXIDE; ACONITUM NAPELLUS ROOT; CLOVE; CINNAMON; GLEDITSIA SINENSIS THORN; GERANIUM WILFORDII WHOLE; CHICKEN BONE; SILYBUM MARIANUM LEAF; COPTIS CHINENSIS ROOT; FRANKINCENSE; MYRRH; ANGELICA DAHURICA VAR. FORMOSANA ROOT; SNOW PEA; ATROPA BELLA-DONNA FLOWERING TOP

Active Ingredient

Menthol 4%

Purpose

Dispelling wind and dampness, promoting blood circulation and relieving pain. Used for rheumatic joints, muscle pain, and sprains.

Use

for external use

Warnings

This product may cause itching, tingling, rash (such as erythema, papules, blisters), local edema, skin ulceration, and in rare cases, systemic discomfort.

Do not use

1. Prohibited for pregnant women.

2. Prohibited for infants and young children.

3. Prohibited for skin ulcers, skin lesions, or infected areas.

4. It is prohibited for those who are allergic to this product and its ingredients (including excipients).

5. It is prohibited for those who are allergic to rubber paste.

When Using

Lingrui Bone Strengthening Musk Pain Relieving Cream needs to be replaced every 24 hours

Stop Use

Itching, tingling, rash (such as erythema, papules, blisters), local edema caused by medication, skin ulceration, etc

Ask Doctor

Diabetes patients ask the doctor

Keep Oot Of Reach Of Children

Please keep this product out of reach of children.

Directions

Apply the adhesive side of the patch to the affected area. Use one patch for up to 8 hours

Inactive ingredients

Inactive ingredients.Raw Cao Wu,Raw Kawashima Frankincense,myrrh,
raw strychnine, cloves, cinnamon, thorns,windbreaks, stork's-bill, incense,
snowdrops, bones
Cortex Eucommiae, Angelica dahurica, Silybum marianum, Dried ginger, Methyl
salicylate
lce chips, camphor, rue infusion, belladonna flowManufactured for
extract. Excipients are: rubber, rosin,
zinc oxide, sheep's .Hair fat, petroleum
jelly, liquid paraffin,Dimethyl Sulfoxide,